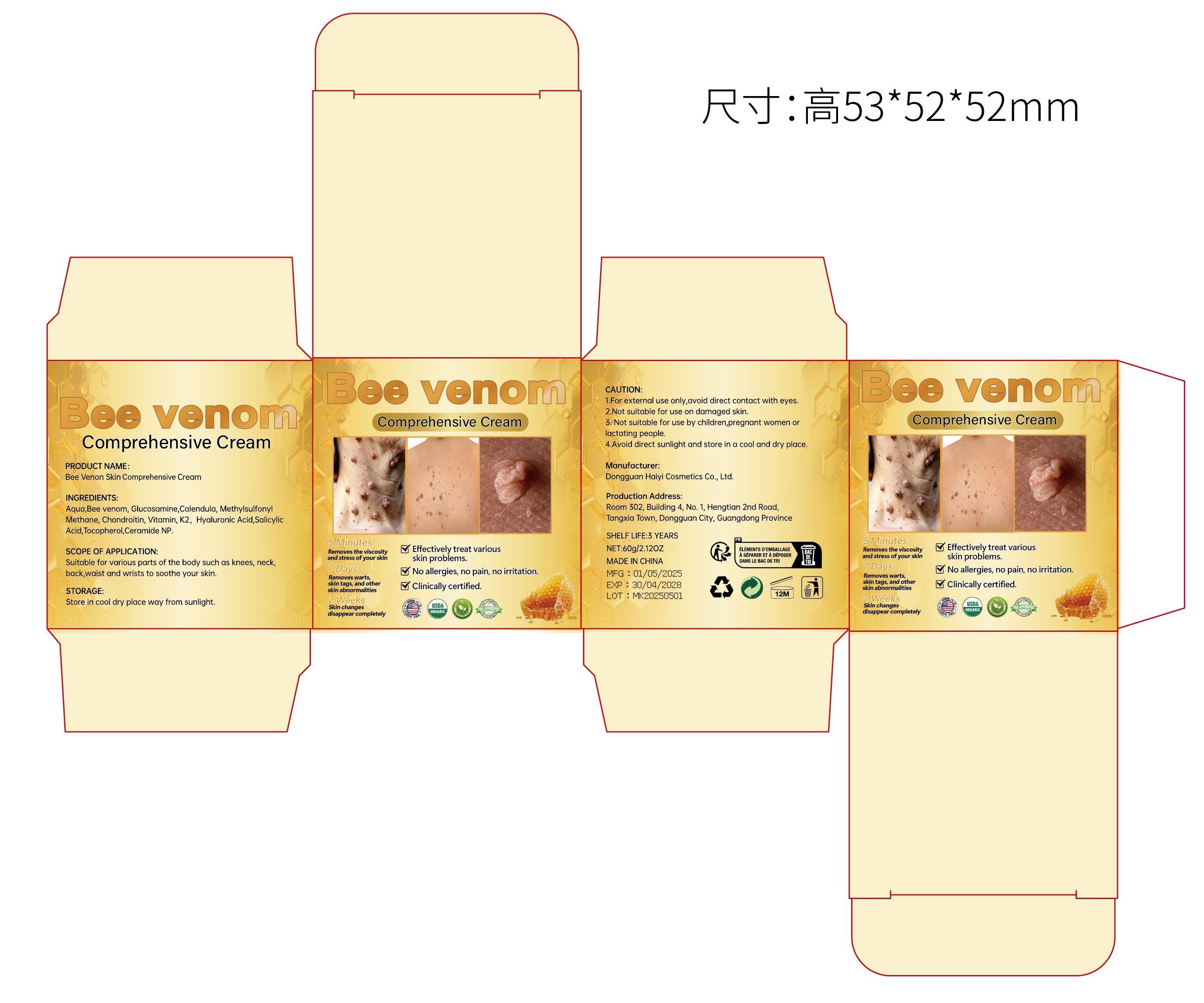 DRUG LABEL: Bee Venon Skin Comprehensive Cream
NDC: 85594-005 | Form: CREAM
Manufacturer: Dongguan Haiyi Cosmetics Co., Ltd.
Category: otc | Type: HUMAN OTC DRUG LABEL
Date: 20250611

ACTIVE INGREDIENTS: BEE POLLEN 5 mg/60 g
INACTIVE INGREDIENTS: HYALURONIC ACID; DIMETHYL SULFONE; CALENDULA OFFICINALIS FLOWER; CERAMIDE NP; CHONDROITIN SULFATE (BOVINE); TOCOPHEROL; MENAQUINONE 7; WATER; SALICYLIC ACID; GLUCOSAMINE

85594-005 Bee Venon Skin Comprehensive Cream

ACTIVE INGREDIENT

Bee Venom

INACTIVE INGREDIENT

Aqua
Glucosamine
Calendula
Methylsulfonyl Methane
Hyaluronic Acid
Ceramide NP
Chondroitin
Tocopherol
Vitamin K2
Salicylic Acid

PURPOSE

5 MinutesRemoves the viscosityand stress of your skin

7 DaysReinoves warts.skin tags, and other skin abnormalities
2 WeeksSkin changesdisappear completely

WARNINGS

1).For external use only, avoid directcontact with eyes, lf you feel any discomfort, stop using itand wash it with plenty of water. In severe cases, pleaseseek medical attention in time.
2). Not allowed to be used on damaged skin,

STOP USE

This product may cause allergic reactions in asmall number of people.
lf you experience any discomfort,please stop using it immediately.

DO NOT USE

Not suitable for use by children, pregnantor breast feeding people.

KEEP OUT OF REACH OF CHILDREN

KEEP THE PRODUCT OUT OF REACH OF CHILDREN to

INDICATIONS AND USAGE

Suitable for various parts of the body such as knees, neck,back,waist and wrists to soothe your skin.

DOSAGE AND ADMINISTRATION

take an appropriateamount,Use 2-3 times a week